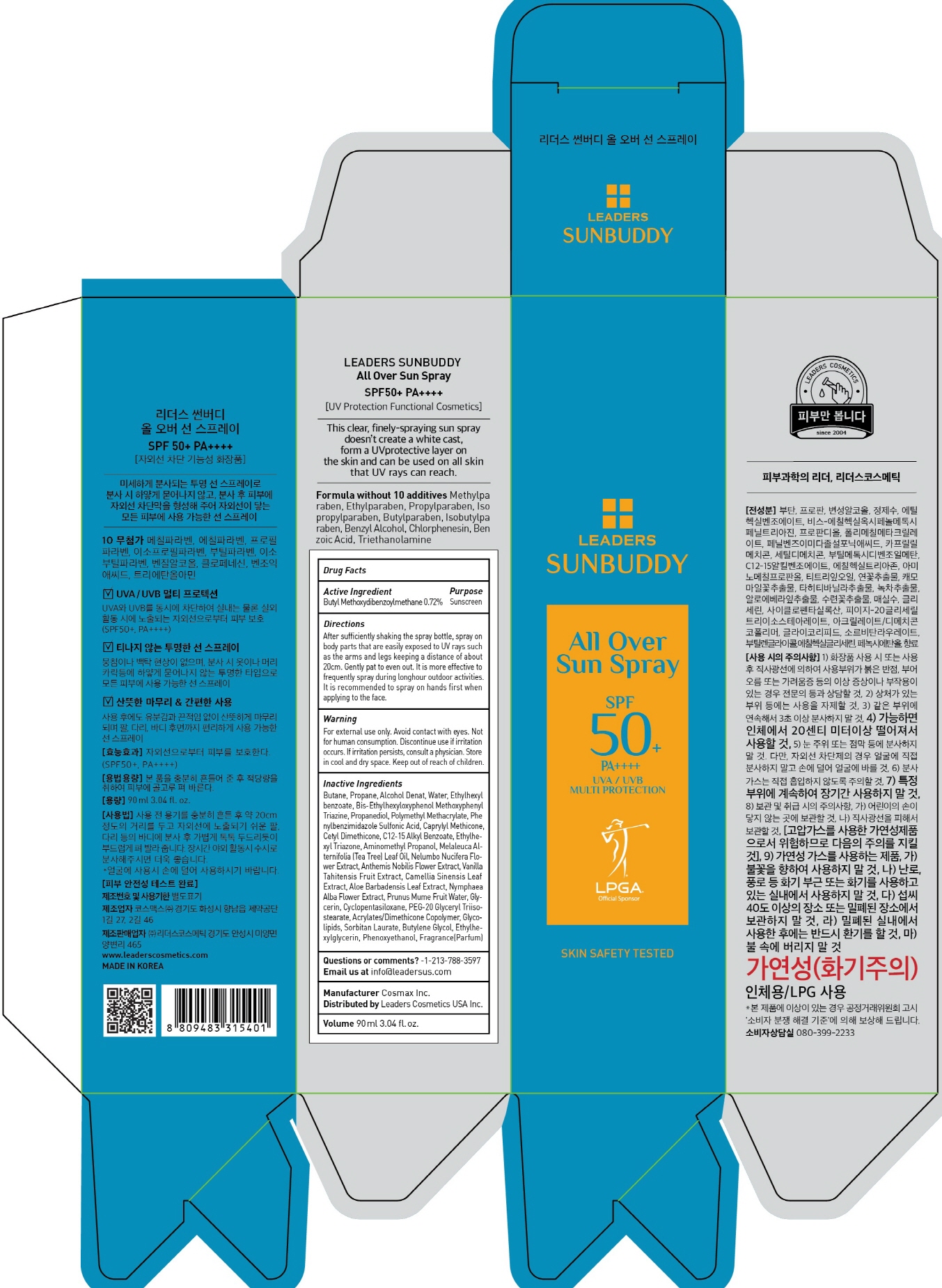 DRUG LABEL: LEADERS SUNBUDDY ALL OVER SUN
NDC: 69424-590 | Form: SPRAY
Manufacturer: LEADERS COSMETICS CO.,LTD.
Category: otc | Type: HUMAN OTC DRUG LABEL
Date: 20170726

ACTIVE INGREDIENTS: AVOBENZONE 0.64 g/90 mL
INACTIVE INGREDIENTS: Butane; Propane

ACTIVE INGREDIENT

Active Ingredient: Butyl Methoxydibenzoylmethane 0.72%

INACTIVE INGREDIENT

Inactive Ingredients: Butane, Propane, Alcohol Denat, Water, Ethylhexyl benzoate, Bis-Ethylhexyloxyphenol Methoxyphenyl Triazine, Propanediol, Polymethyl Methacrylate, Phenylbenzimidazole Sulfonic Acid, Caprylyl Methicone, Cetyl Dimethicone, C12-15 Alkyl Benzoate, Ethylhexyl Triazone, Aminomethyl Propanol, Melaleuca Alternifolia (Tea Tree) Leaf Oil, Nelumbo Nucifera Flower Extract, Anthemis Nobilis Flower Extract, Vanilla Tahitensis Fruit Extract, Camellia Sinensis Leaf Extract, Aloe Barbadensis Leaf Extract, Nymphaea Alba Flower Extract, Prunus Mume Fruit Water, Glycerin, Cyclopentasiloxane, PEG-20 Glyceryl Triisostearate, Acrylates/Dimethicone Copolymer, Glycolipids, Sorbitan Laurate, Butylene Glycol, Ethylhexylglycerin, Phenoxyethanol, Fragrance(Parfum)

PURPOSE

Purpose: Sunscreen

WARNINGS

Warning: For external use only. Avoid contact with eyes. Not for human consumption. Discontinue use if irritation occurs. If irritation persists, consult a physician. Store in cool and dry space. Keep out of reach of children.

DESCRIPTION

Directions: After sufficiently shaking the spray bottle, spray on body parts that are easily exposed to UV rays such as the arms and legs keeping a distance of about 20cm. Gently pat to even out. It is more effective to frequently spray during long-hour outdoor activities. It is recommended to spray on hands first when applying to the face.

Questions or comments? -1-213-788-3597

Email us at info@leadersus.com